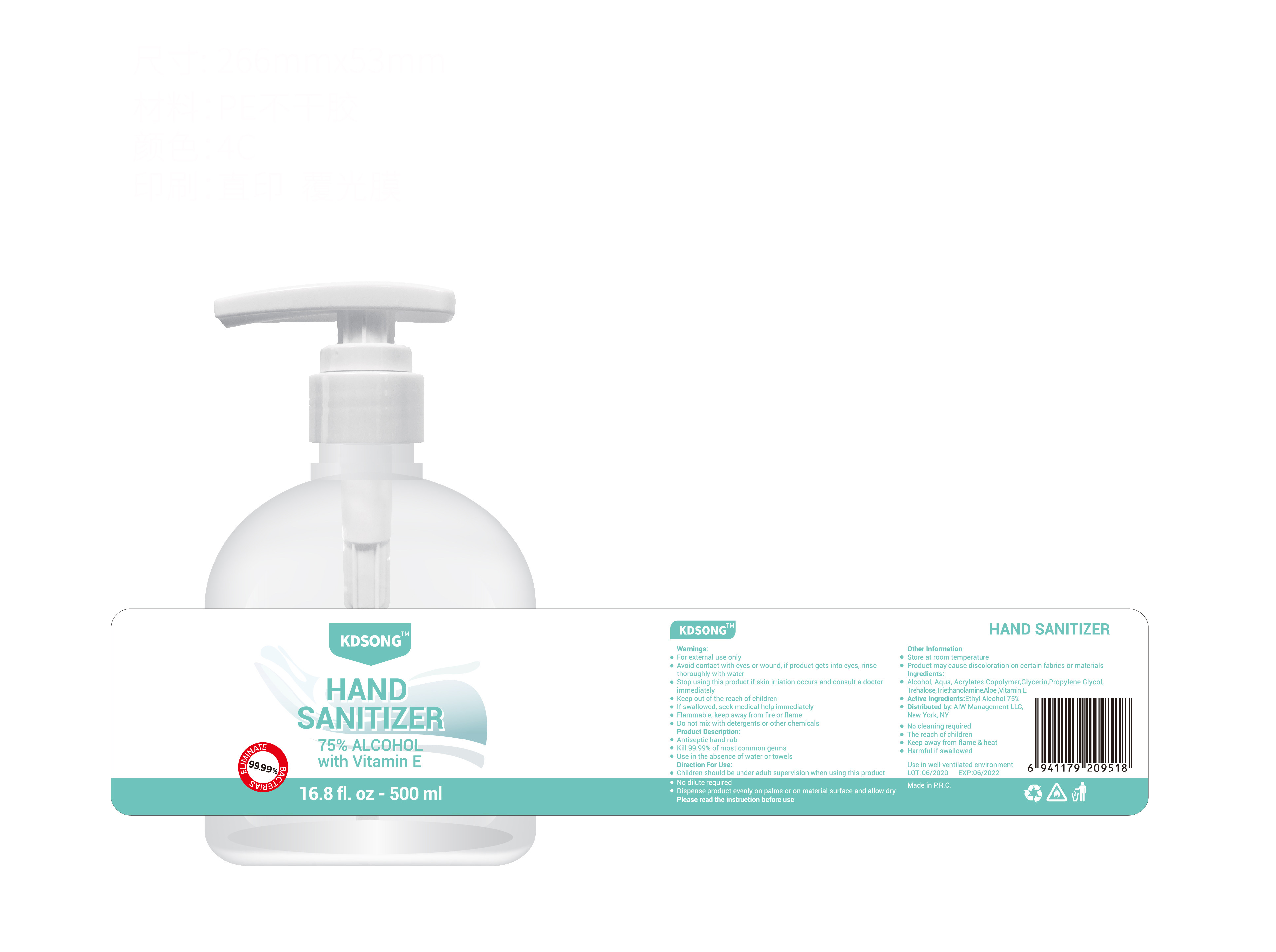 DRUG LABEL: HAND SANIZITER
NDC: 54457-009 | Form: LIQUID
Manufacturer: GUANGZHOU ZUNAI DAILY COSMETICS CO., LTD
Category: otc | Type: HUMAN OTC DRUG LABEL
Date: 20200612

ACTIVE INGREDIENTS: ALCOHOL 375 mL/500 mL
INACTIVE INGREDIENTS: TREHALOSE; TROLAMINE; BUTYL ACRYLATE/METHYL METHACRYLATE/METHACRYLIC ACID COPOLYMER (18000 MW); GLYCERIN; WATER; PROPYLENE GLYCOL

DOSAGE AND ADMINISTRATION

Store at room temperature

INACTIVE INGREDIENT

AQUA，ACRYLATES COPOLYMER，GLYCERIN，PROPYLENE GLYCOL，TREHALOSE，TRIETHANOLAMINE

INDICATIONS AND USAGE

Place enough product on your hands to cover all suraces.Rub hands together until dry.

ACTIVE INGREDIENT

ALCOHOL

keep out of reach of children

PURPOSE

Disinfection
Sterilization
No Rinseing

WARNINGS

●For external use only,Avoid contact with eyes or wound, if product gets into eyes, rinse thoroughly with water
●Stop using this product if skin irriation occurs and consult a doctor immediately
●Keep out of the reach of children
●If swallowed, seek medical help immediately
●Flammable, keep away from fire or flame
●Do not mix with detergents or other chemicals